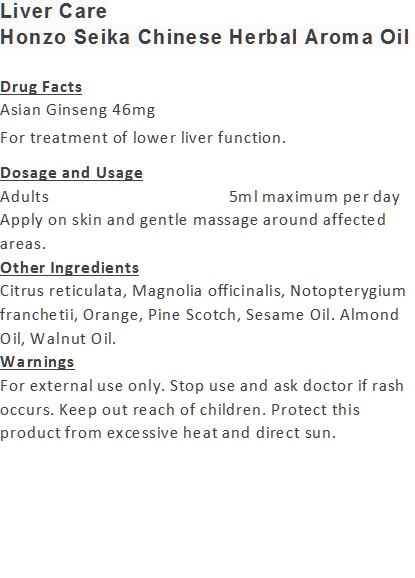 DRUG LABEL: Liver Care
NDC: 70470-9931 | Form: OIL
Manufacturer: Phytopia Co., Ltd.
Category: otc | Type: HUMAN OTC DRUG LABEL
Date: 20170101

ACTIVE INGREDIENTS: ASIAN GINSENG 46 mg/100 mL
INACTIVE INGREDIENTS: ALMOND OIL; ORANGE OIL; CITRUS RETICULATA FRUIT OIL; WALNUT OIL; SESAME OIL; NOTOPTERYGIUM FRANCHETII ROOT; PINUS SYLVESTRIS BARK; MAGNOLIA OFFICINALIS FLOWER

Drug Facts

Asian Ginseng 46mg

Use

For treatment of lower liver function.

Dosage Suggestion

Adults 5ml maximum per day

INACTIVE INGREDIENT

Other Ingredients

Citrus reticulata, Magnolia officinalis, Notopterygium franchetii, Orange, Pine Scotch, Sesame Oil. Almond Oil, Walnut Oil.

Directions

Apply on skin and gentle massage around affected area.

Warnings

For external use only. Stop use and ask doctor if rash occurs. Keep out reach of children.

Other Information

Protect this product from excessive heat

and direct sun.

Warnings

For external use only. Stop use and ask doctor if rash occurs. Keep out reach of children.